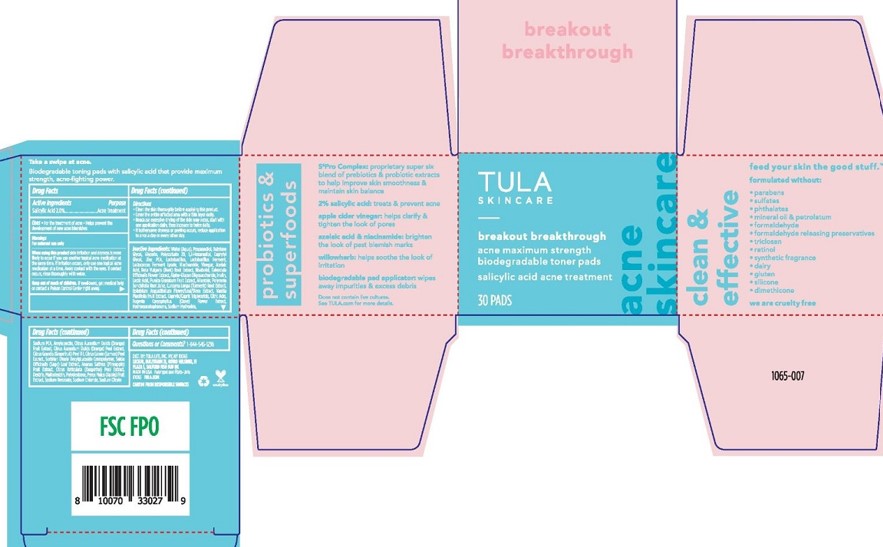 DRUG LABEL: TULA SKINCARE BREAKOUT BREAKTHROUGH ACNE TONER PADS
NDC: 84126-152 | Form: DISC
Manufacturer: The Procter & Gamble Manufacturing Company
Category: otc | Type: HUMAN OTC DRUG LABEL
Date: 20250603

ACTIVE INGREDIENTS: SALICYLIC ACID 2 g/100 1
INACTIVE INGREDIENTS: CAPRYLYL GLYCOL; ALLANTOIN; SODIUM HYDROXIDE; GLYCERIN; MALTODEXTRIN; CITRUS AURANTIUM DULCIS (ORANGE) PEEL POWDER; PYRUS MALUS (APPLE) FRUIT; AMYLOPECTIN, UNSPECIFIED SOURCE; CAPRYLIC/CAPRIC TRIGLYCERIDE; CITRUS TANGERINA (TANGERINE) PEEL; CURCUMA LONGA (TURMERIC) ROOT; 1,2-HEXANEDIOL; CLOVE; POMEGRANATE; LACTIC ACID; ANANAS SATIVUS (PINEAPPLE) FRUIT; NIACINAMIDE; CITRUS LIMON (LEMON) PEEL; HYDROXYACETOPHENONE; SODIUM BENZOATE; SODIUM CITRATE; PROPANEDIOL; POLYDEXTROSE; BETA VULGARIS (BEET) ROOT JUICE; CALENDULA OFFICINALIS FLOWER; CITRUS GRANDIS (GRAPEFRUIT) PEEL OIL; CITRIC ACID; ORANGE; POLYMNIA SONCHIFOLIA ROOT JUICE; SORBITAN OLEATE DECYLGLUCOSIDE CROSSPOLYMER; ACETIC ACID; EPILOBIUM ANGUSTIFOLIUM FLOWERING TOP; INULIN; BUTYLENE GLYCOL; BISABOLOL; SODIUM PCA; VANILLA PLANIFOLIA FRUIT; LACTOBACILLUS; ALPHA-GLUCAN OLIGOSACCHARIDE; SAGE; POLYSORBATE 20; WATER; SODIUM CHLORIDE; AZELAIC ACID; ZINC PCA

ACTIVE INGREDIENT

Salicylic Acid 2.0%

PURPOSE

Acne Treatment

Uses

For the treatment of acne. Helps prevent the development of new blemishes.

Warnings

For external use only

When using this product

- skin irritation and dryness is more likely to occur if you use another topical acne medication at the same time. If irritation occurs, only use one topical acne medication at a time.
- Avoid contact with the eyes. If contact occurs, rinse thoroughly with water.

Keep out of reach of children. If swallowed, get medical help or contact a Poison Control Center right away.

Direction

• Clean the skin thoroughly before applying this product.
• Cover the entire affected area with a thin layer daily.
• Because excessive drying of the skin may occur, start with one application daily, then increase to twice daily.
• If bothersome dryness or peeling occurs, reduce application to once a day or every other day.

INACTIVE INGREDIENT

WATER (AQUA), PROPANEDIOL, BUTYLENE GLYCOL, GLYCERIN, POLYSORBATE 20, 1,2- HEXANEDIOL, CAPRYLYL GLYCOL, ZINC PCA, LACTOBACILLUS, LACTOBACILLUS FERMENT, LACTOCOCCUS FERMENT LYSATE, NIACINAMIDE, VINEGAR, AZELAIC ACID, BETA VULGARIS (BEET) ROOT EXTRACT, BISABOLOL, CALENDULA OFFICINALIS FLOWER EXTRACT, ALPHA-GLUCAN OLIGOSACCHARIDE, INULIN, LACTIC ACID, PUNICA GRANATUM FRUIT EXTRACT, ALLANTOIN, POLYMNIA SONCHIFOLIA ROOT JUICE, CURCUMA LONGA (TURMERIC) ROOT EXTRACT, EPILOBIUM ANGUSTIFOLIUM FLOWER/LEAF/STEM EXTRACT, VANILLA PLANIFOLIA FRUIT EXTRACT, CAPRYLIC/CAPRIC TRIGLYCERIDE, CITRIC ACID, EUGENIA CARYOPHYLLUS (CLOVE) FLOWER EXTRACT, HYDROXYACETOPHENONE, SODIUM HYDROXIDE, SODIUM PCA, AMYLOPECTIN, CITRUS AURANTIUM DULCIS (ORANGE) FRUIT EXTRACT, CITRUS AURANTIUM DULCIS (ORANGE) PEEL EXTRACT, CITRUS GRANDIS (GRAPEFRUIT) PEEL OIL, CITRUS LIMON (LEMON) PEEL EXTRACT, SORBITAN OLEATE DECYLGLUCOSIDE CROSSPOLYMER, SALVIA OFFICINALIS (SAGE) LEAF EXTRACT, ANANAS SATIVUS (PINEAPPLE) FRUIT EXTRACT, CITRUS RETICULATA (TANGERINE) PEEL EXTRACT, DEXTRIN, MALTODEXTRIN, POLYDEXTROSE, PYRUS MALUS (APPLE) FRUIT EXTRACT, SODIUM BENZOATE, SODIUM CHLORIDE, SODIUM CITRATE.

Questions or Comments?

1-844-545-1236

DIST BY TULA LIFE, INC. NY, NY 10065

PACKAGE LABEL

TULA

SKINCARE

breakout breakthrough

acne clarifying maximum strength

biodegradable toner pads

salicyclic acid acne treatment

30 pads